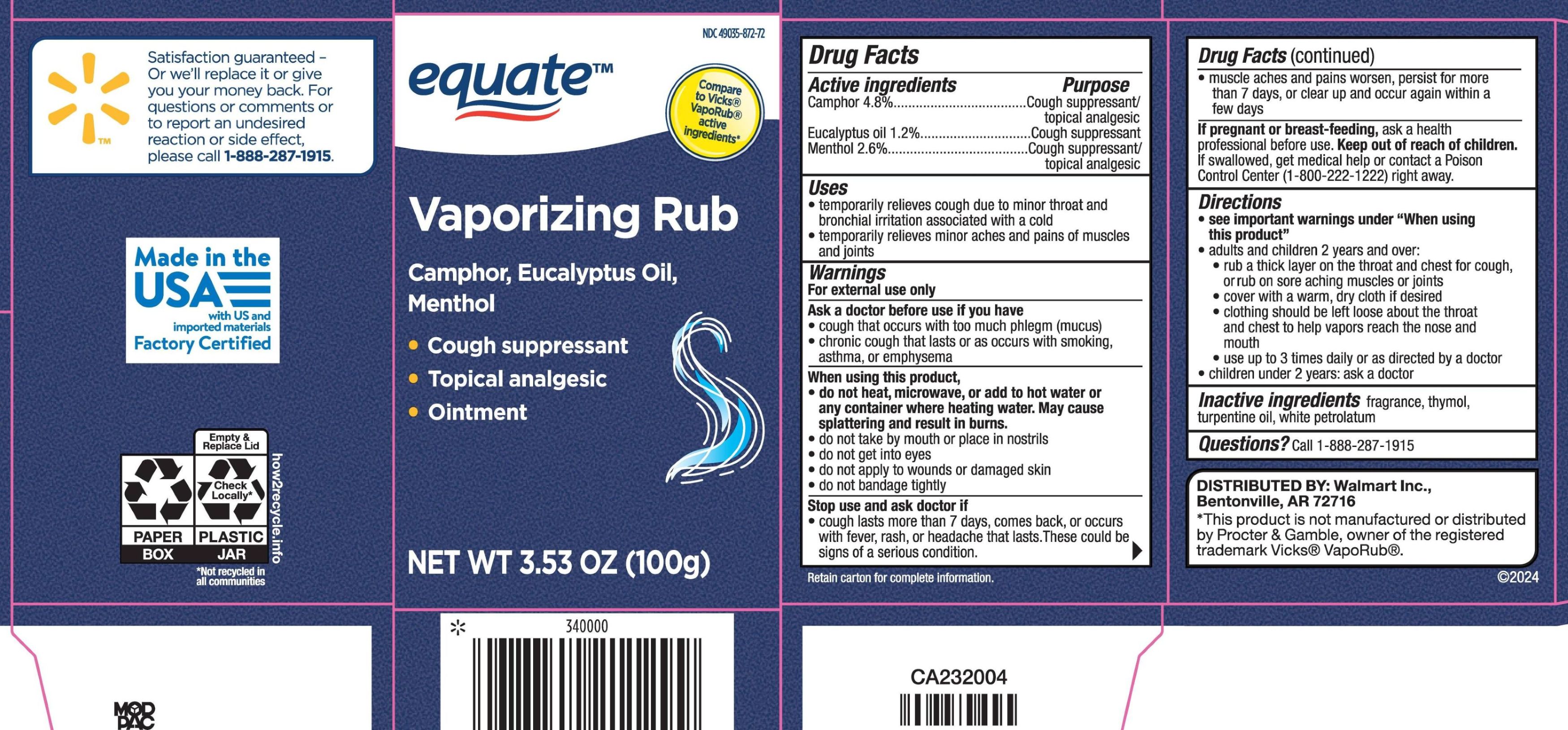 DRUG LABEL: Equate Vaporizing
NDC: 49035-872 | Form: OINTMENT
Manufacturer: Wal-Mart Stores Inc
Category: otc | Type: HUMAN OTC DRUG LABEL
Date: 20260223

ACTIVE INGREDIENTS: CAMPHOR (SYNTHETIC) 48 mg/1 g; EUCALYPTUS OIL 12 mg/1 g; MENTHOL, UNSPECIFIED FORM 26 mg/1 g
INACTIVE INGREDIENTS: TURPENTINE; PETROLATUM; THYMOL

Drug Facts - Equate Vaporizing Rub

Active ingredients

Camphor 4.8%

Eucalyptus oil 1.2%

Menthol 2.6%

Purpose

Camphor - Cough suppressant / topical analgesic

Eucalyptus oil - Cough suppressant

Menthol - Cough suppressant / topical analgesic

Uses

- temporarily relieves cough due to minor throat and bronchial irritation associated with a cold
- temporarily relieves minor aches and pains of muscles and joints

Warnings

For external use only

Ask a doctor before use if you have

- cough that occurs with too much phlegm (mucus)
- chronic cough that lasts or occurs with smoking, asthma, or emphysema

When using this product

- do not heat
- do not microwave
- do not add to hot water or any container where heating water. May cause splattering and result in burns.
- do not take by mouth or place in nostrils
- do not get into eyes
- do not apply to wounds or damaged skin
- do not bandage tightly

Stop use and ask a doctor if

- cough lasts more than 7 days, comes back, or occurs with fever, rash, or headache that lasts. These could be signs of a serious condition.
- muscle aches and pains worsen, persist for more than 7 days, or clear up and occur again within a few days

If pregnant or breast-feeding,

ask a health professional before use.

Keep out of reach of children.

If swallowed, get medical help or contact a Poison Control Center right away.

Directions

- see important warning under "When using this product"
- adults and children 2 years and over:
- rub a thick layer on the throat and chest for cough, or rub on sore aching muscles and joints
- cover with a warm, dry cloth if desired
- clothing should be left loose about the throat and chest to help vapors reach the nose and mouth
- use up to 3 times daily, or as directed by a doctor
- children under 2 years: ask a doctor

Inactive ingredients

fragrance, thymol, turpentine oil, white petrolatum

Questions?

Call: 1-888-287-1915